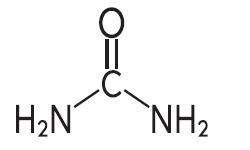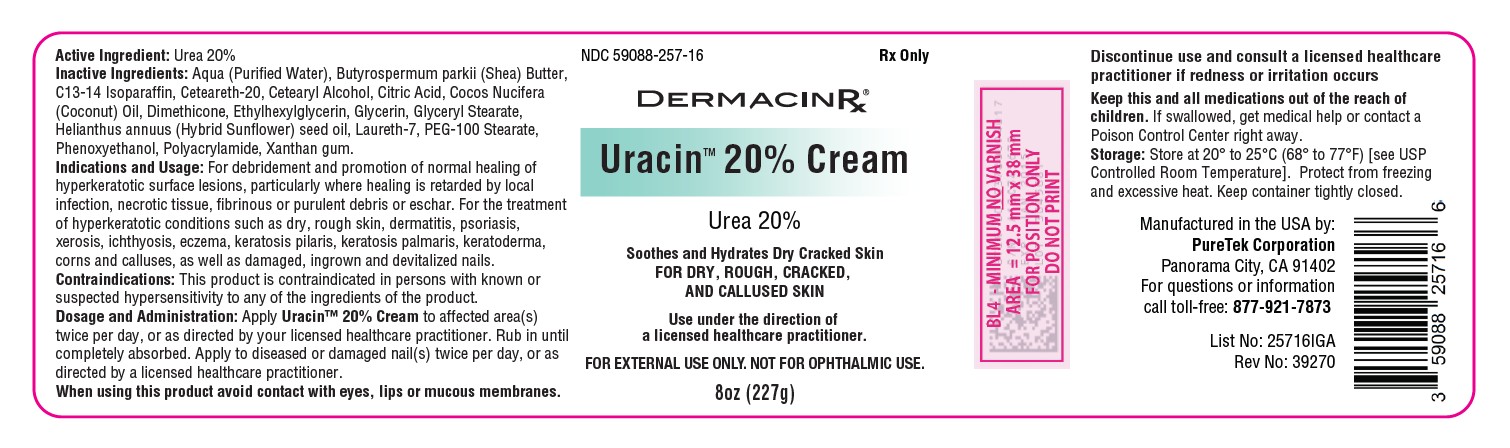 DRUG LABEL: Uracin 20%
NDC: 59088-257 | Form: CREAM
Manufacturer: PureTek Corporation
Category: prescription | Type: HUMAN PRESCRIPTION DRUG LABEL
Date: 20260220

ACTIVE INGREDIENTS: UREA 0.2 g/1 g
INACTIVE INGREDIENTS: CITRIC ACID; CETEARETH-20; BUTYROSPERMUM PARKII (SHEA) BUTTER; COCOS NUCIFERA (COCONUT) OIL; PEG-100 STEARATE; GLYCERIN; PHENOXYETHANOL; CETEARYL ALCOHOL; GLYCERYL STEARATE; XANTHAN GUM; HELIANTHUS ANNUUS (SUNFLOWER) SEED OIL; WATER; LAURETH-7; C13-14 ISOPARAFFIN; DIMETHICONE 350; ETHYLHEXYLGLYCERIN; ACRYLAMIDE/SODIUM ACRYLOYLDIMETHYLTAURATE COPOLYMER (120000 MPA.S AT 1%)

Uracin 20% Cream
Rx only
FOR EXTERNAL USE ONLY. NOT FOR OPHTHALMIC USE.

DESCRIPTION

Uracin 20% Cream is a keratolytic emollient which is a gentle, yet potent, tissue softener for nails and/or skin. Each gram contains 200 mg of urea in a vehicle consisting of the following inactive ingredients : Aqua (Purified Water), Butyrospermum Parkii (Shea) Butter, C13-14 Isoparaffin, Ceteareth-20, Cetearyl Alcohol, Citric Acid, Cocos Nucifera (Coconut) Oil, Dimethicone, Ethylhexylglycerin, Glycerin, Glyceryl Stearate, Helianthus Annuus (Sunflower) Seed Oil, Laureth-7, PEG-100 Stearate, Phenoxyethanol, Polyacrylamide, Xanthan Gum.

Urea is a diamide of carbonic acid with the following chemical structure:

CLINICAL PHARMACOLOGY

Urea gently dissolves the intracellular matrix which results in loosening of the horny layer of the skin and shedding of scaly skin at regular intervals, thereby softening hyperkeratotic areas of the skin.

Pharmacokinetics

The mechanism of action of topically applied urea is not yet known.

INDICATIONS AND USAGE

For debridement and promotion of normal healing of hyperkeratotic surface lesions, particularly where healing is retarded by local infection, necrotic tissue, ﬁbrinous or purulent debris or eschar. Urea is useful for the treatment of hyperkeratotic conditions such as dry, rough skin, dermatitis, psoriasis, xerosis, ichthyosis, eczema, keratosis pilaris, keratosis palmaris, keratoderma, corns and calluses, as well as damaged, ingrown and devitalized nails. Soothes rough and dry skin.

CONTRAINDICATIONS

This product is contraindicated in persons with known or suspected hypersensitivity to any of the ingredients of the product.

WARNINGS

FOR EXTERNAL USE ONLY. NOT FOR OPHTHALMIC USE.

KEEP THIS AND ALL MEDICATIONS OUT OF THE REACH OF CHILDREN.

If swallowed, get medical help or contact a Poison Control Center right away.

Avoid contact with eyes, lips and mucous membranes.

General

This product is to be used as directed by a licensed healthcare practitioner and should not be used to treat any condition other than that for which it was prescribed. If redness or irritation occurs, discontinue use and consult a licensed healthcare practitioner.

Information for Patients

Patients should discontinue the use of this product if the condition becomes worse or if a rash develops in the area being treated or elsewhere. Avoid contact with eyes, lips and mucous membranes.

Carcinogenesis, Mutagenesis and Impairment of Fertility:

Long-term animal studies for carcinogenic potential have not been performed on this product to date. Studies on reproduction and fertility also have not been performed.

Pregnancy:

Category C. Animal reproduction studies have not been conducted with this product. It is also not known whether this product can affect reproduction capacity or cause fetal harm when administered to a pregnant woman. This product should be used by a pregnant woman only if clearly needed or when potential benefits outweigh potential hazards to the fetus.

Nursing Mothers:

It is not known whether this drug is excreted in human milk. Because many drugs are excreted in human milk, caution should be exercised when this product is administered to a nursing woman.

ADVERSE REACTIONS:

Transient stinging, burning, itching or irritation may occur and normally disappear upon discontinuing the use of this product.

DOSAGE AND ADMINISTRATION

Apply Uracin 20% Cream to affected area twice per day, or as directed by a licensed healthcare practitioner.

Rub in until completely absorbed.

Apply to diseased or damaged nail(s) twice per day, or as directed by a licensed healthcare practitioner.

HOW SUPPLIED

Uracin™ 20% cream is supplied in a 8 oz.(227 g) jar, NDC 59088-257-16

STORAGE

Store at 20° to 25°C (68° to 77°F) [see USP Controlled Room Temperature].

Protect from freezing and excessive heat. Keep container tightly closed.

To report side effects, call PureTek Corporation at 1-877-921-7873.

Uracin™ 20% Cream

Manufactured in the USA by:
PureTek Corporation
Panorama City, CA 91402
For questions or information
call toll-free: 877-921-7873